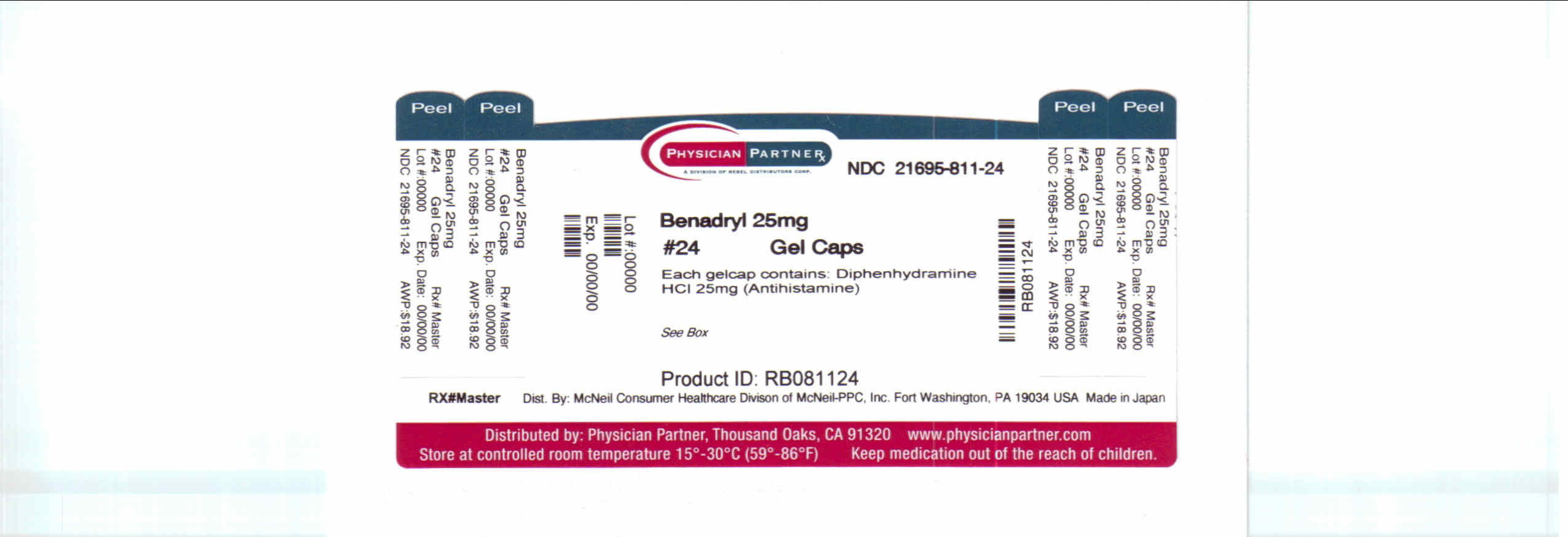 DRUG LABEL: Benadryl
NDC: 21695-811 | Form: TABLET, COATED
Manufacturer: Rebel Distributors Corp
Category: otc | Type: HUMAN OTC DRUG LABEL
Date: 20110413

ACTIVE INGREDIENTS: Diphenhydramine Hydrochloride 25 mg/1 1
INACTIVE INGREDIENTS: butylparaben

Benadryl®™
ALLERGY

Drug Facts

Active ingredient (in each gelcap)

Diphenhydramine HCl 25 mg

Purpose

Antihistamine

Uses

- temporarily relieves these symptoms due to hay fever or other upper respiratory allergies:
  - runny nose
  - sneezing
  - itchy, watery eyes
  - itching of the nose or throat
- temporarily relieves these symptoms due to the common cold:
  - runny nose
  - sneezing

Warnings

Do not use

- to make a child sleepy
- with any other product containing diphenhydramine, even one used on skin

Ask a doctor before use if you have

- glaucoma
- trouble urinating due to an enlarged prostate gland
- a breathing problem such as emphysema or chronic bronchitis

Ask a doctor or pharmacist before use if you are taking sedatives or tranquilizers

When using this product

- marked drowsiness may occur
- avoid alcoholic drinks
- alcohol, sedatives, and tranquilizers may increase drowsiness
- be careful when driving a motor vehicle or operating machinery
- excitability may occur, especially in children

PREGNANCY OR BREAST FEEDING

If pregnant or breast-feeding, ask a health professional before use.

Keep out of reach of children. In case of overdose, get medical help or contact a Poison Control Center right away. (1-800-222-1222)

Directions

- if needed, repeat dose every 4 to 6 hours
- do not take more than 6 times in 24 hours

adults and children 12 years of age and over | 1 to 2 gelcaps
children 6 to under 12 years of age | 1 gelcap
children under 6 years of age | do not use this product in children under 6 years of age

Other information

- each gelcap contains: calcium 35 mg
- store between 20-25°C (68-77°F). Avoid high humidity.
- do not use if carton is open or if blister unit is broken
- see side panel for lot number and expiration date

Inactive ingredients

benzyl alcohol, black iron oxide, butylparaben, carboxymethylcellulose sodium, crospovidone, D&C red #28, dibasic calcium phosphate dihydrate, edetate calcium disodium, FD&C red #40, gelatin, hypromellose, magnesium stearate, methylparaben, microcrystalline cellulose, polyethylene glycol, polysorbate 80, propylparaben, red iron oxide, sodium lauryl sulfate, sodium propionate, titanium dioxide, yellow iron oxide

Questions or comments?

call 1-877-717-2824